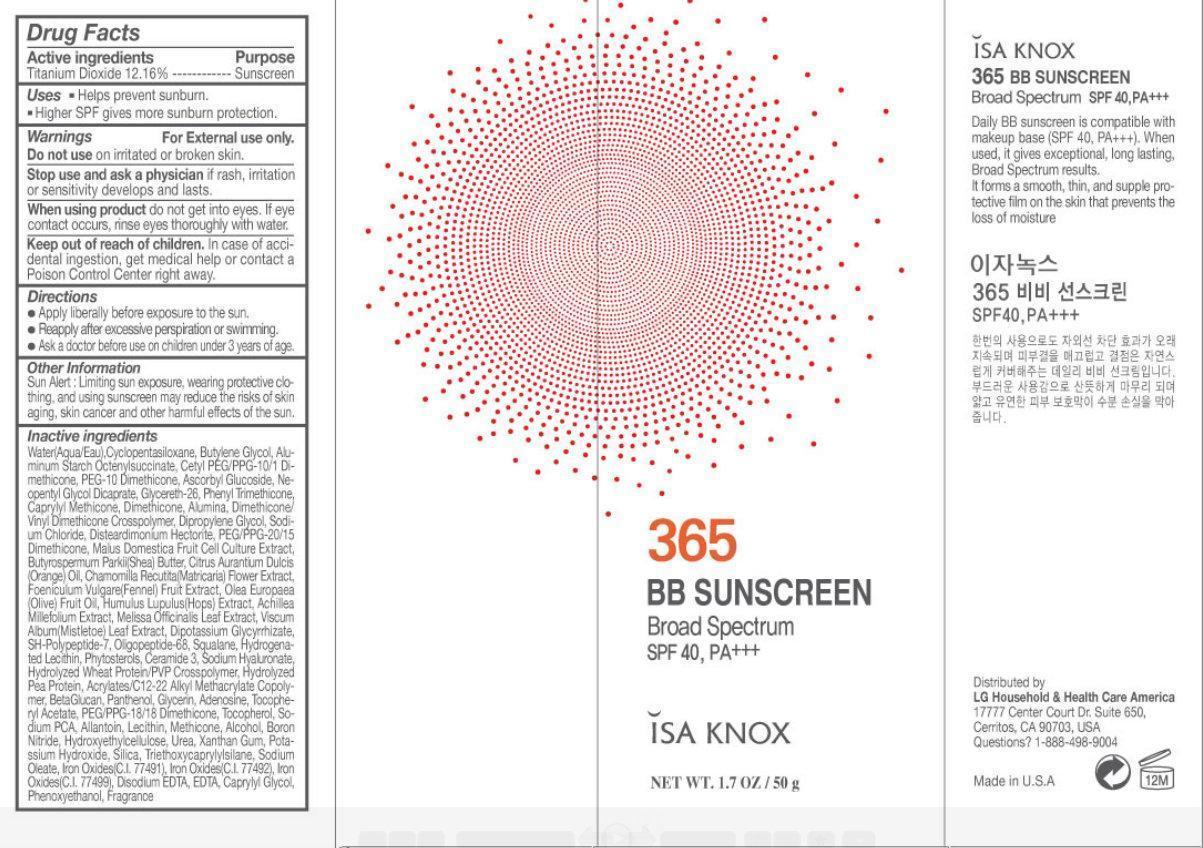 DRUG LABEL: ISA KNOX 365 BB SUNSCREEN Broad Spectrum SPF 40, PA
NDC: 53208-000 | Form: CREAM
Manufacturer: LG Household and Healthcare, Inc.
Category: otc | Type: HUMAN OTC DRUG LABEL
Date: 20260123

ACTIVE INGREDIENTS: TITANIUM DIOXIDE 121.6 mg/1 g
INACTIVE INGREDIENTS: WATER; CYCLOMETHICONE 5; BUTYLENE GLYCOL; ALUMINUM STARCH OCTENYLSUCCINATE; ASCORBYL GLUCOSIDE; NEOPENTYL GLYCOL DICAPRATE; GLYCERETH-26; PHENYL TRIMETHICONE; CAPRYLYL TRISILOXANE; DIMETHICONE; ALUMINUM OXIDE; DIPROPYLENE GLYCOL; SODIUM CHLORIDE; DISTEARDIMONIUM HECTORITE; PEG/PPG-20/15 DIMETHICONE; ORANGE OIL; SHEA BUTTER; CHAMOMILE; FENNEL SEED; OLIVE OIL; HOPS; ACHILLEA MILLEFOLIUM; MELISSA OFFICINALIS LEAF; VISCUM ALBUM FRUITING TOP; GLYCYRRHIZINATE DIPOTASSIUM; SQUALANE; CERAMIDE 3; HYALURONATE SODIUM; PANTHENOL; GLYCERIN; ADENOSINE; .ALPHA.-TOCOPHEROL ACETATE; PEG/PPG-18/18 DIMETHICONE; TOCOPHEROL; SODIUM PYRROLIDONE CARBOXYLATE; ALLANTOIN; ALCOHOL; BORON NITRIDE; UREA; XANTHAN GUM; POTASSIUM HYDROXIDE; SILICON DIOXIDE; TRIETHOXYCAPRYLYLSILANE; SODIUM OLEATE; FERRIC OXIDE RED; FERRIC OXIDE YELLOW; FERROSOFERRIC OXIDE; EDETATE DISODIUM; EDETIC ACID; CAPRYLYL GLYCOL; PHENOXYETHANOL

ISA KNOX 365 BB SUNSCREEN Broad Spectrum SPF 40, PA

Active ingredients

Titanium Dioxide 12.16%

Purpose

Sunscreen

Uses

- Helps prevent sunburn.
- Higher SPF gives more sunburn protection.

Warnings

For External use only.

Do not use

on irritated or broken skin.

Stop use and ask a physician

if rash, irritation or sensitivity develops and lasts.

When using product

do not get into eyes. If eye contact occurs, rinse eyes thoroughly with water.

Keep out of reach of children.

In case of accidental ingestion, get medical help or contact a Poison Control Center right away.

Directions

- Apply liberally before exposure to the sun.
- Reapply after excessive perspiration or swimming.
- Ask a doctor before use on children under 3 years of age.

Other information

Sun Alert: Limiting sun exposure, wearing protective clothing, and using sunscreen may reduce the risks of skin aging, skin cancer and other harmful effects of the sun.

Inactive ingredients

Water(Aqua/Eau), Cyclopentasiloxane, Butylene Glycol, Aluminum Starch Octenylsuccinate, Cetyl PEG/PPG-10/1 Dimethicone, PEG-10 Dimethicone, Ascorbyl Glucoside, Neopentyl Glycol Dicaprate, Glycereth-26, Phenyl Trimethicone, Caprylyl Methicone, Dimethicone, Alumina, Dimethicone Vinyl Dimethicone Crosspolymer, Dipropylene Glycol, Sodium Chloride, Disteardimonium Hectorite, PEG/PPG-20/15 Dimethicone, Malus Domestica Fruit Cell Culture Extract, Butyrospermum Parkii (Shea) Butter, Citrus Aurantium Dulcis (Orange) Oil, Chamomilla Recutita (Matricaria) Flower Extract, Foeniculum Vulgare (Fennel) Fruit Extract, Olea Europaea (Olive) Fruit Oil, Humulus Lupulus (Hops) Extract, Achillea Millefolium Extract, Melissa Officinalis Leaf Extract, Viscum Album (Mistletoe) Leaf Extract, Dipotassium Glycyrrhizate, SH-Polypeptide-7, Oligopeptide-68, Squalane, Hydrogenated Lecithin, Phytosterols, Ceramide 3, Sodium Hyaluronate, Hydrolyzed Wheat Protein/PVP Crosspolymer, Hydrolyzed Pea Protein, Acrylates/C12-22 Alkyl Methacrylate Copolymer, BetaGlucan, Panthenol, Glycerin, Adenosine, Tocopheryl Acetate, PEG/PPG-18/18 Dimethicone, Tocopherol, Sodium PCA, Allantoin, Lecithin, Methicone, Alcohol, Boron Nitride, Hydroxyethylcellulose, Urea, Xanthan Gum, Potassium Hydroxide, Silica, Triethoxycaprylylsilane, Sodium Oleate, Iron Oxides (C.I. 77491), Iron Oxides (C.I. 77492), Iron Oxides (C.I. 77499), Disodium EDTA, EDTA, Caprylyl Glycol, Phenoxyethanol, Fragrance.

ISA KNOX 365 BB SUNSCREEN Broad Spectrum SPF 40, PA

Daily BB sunscreen is compatible with makeup base (SPF 40, PA+++). When used, it gives exceptional, long lasting, Broad Spectrum results. It forms a smooth, thin, and supple protective film on the skin that prevents the loss of moisture Distributed by 17777 Center Court Dr. Suite 650, Cerritos, CA 90703, USA Questions? 1-888-498-9004 Made in U.S.A.
LG Household and Health Care America

PACKAGE LABEL

365 BB SUNSCREEN Broad Spectrum SPF 40, PA+++ ISA KNOX NET WT. 1.7 OZ / 50 g